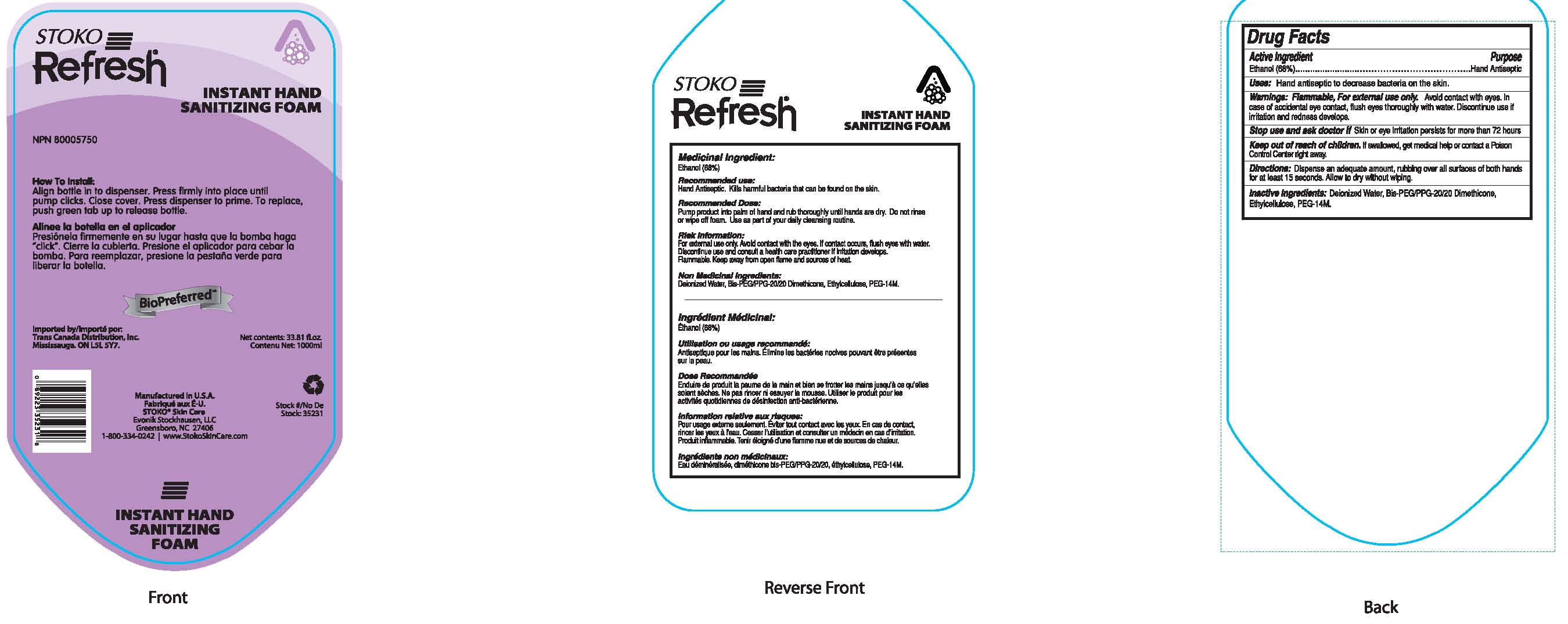 DRUG LABEL: Refresh Foaming Instant Hand Sanitizer
NDC: 64064-050 | Form: LIQUID
Manufacturer: Evonik Stockhausen, LLC
Category: otc | Type: HUMAN OTC DRUG LABEL
Date: 20111026

ACTIVE INGREDIENTS: ALCOHOL 68 mL/100 mL
INACTIVE INGREDIENTS: WATER; POLYETHYLENE GLYCOL 14000; ETHYLCELLULOSES

Drug Facts

ACTIVE INGREDIENT

Ethanol (68%)

PURPOSE

Antiseptic

INDICATIONS AND USAGE

Kills harmful bacteria that can be found on the skin.

WARNINGS

Flammable. For external use only. Avoid contact with eyes.
In case of accidental eye contact, flush eyes thoroughly with water.

Stop use and ask a doctor if skin or eye irritation persists for more than 72 hours..

Keep out of reach of children. If swallowed, get medical help or contact a Poison Control Center right away.

DOSAGE AND ADMINISTRATION

Pump product in palm of hand and rub thoroughly until hands are dry. Do not rinse or wipe off foam.

INACTIVE INGREDIENT

Deionized water, Bis-PEG/PPG-20/20 Dimethicone, ethylcellulose, PEG-14M

PACKAGE LABEL

Stoko Refresh

Instant Hand Sanitizer Foam

NPN 80005750

Imported by / Importe par:

Trans Canada Distribution Inc.,

Mississauga, ON L5L 5Y7

Net Contents 33.8 fl.oz.
Contenu Net: 1000ml

Manufactured in USA

Fabrique aux E-U.

Stoko Skin Care

Evonik Stockhausen, LLC

Greensboro, NC 27406

1-800-334-0242 www.StokoSkinCare.com

Stock #/No De Stock: 35231

Discontinue use if irritation and redness develops.